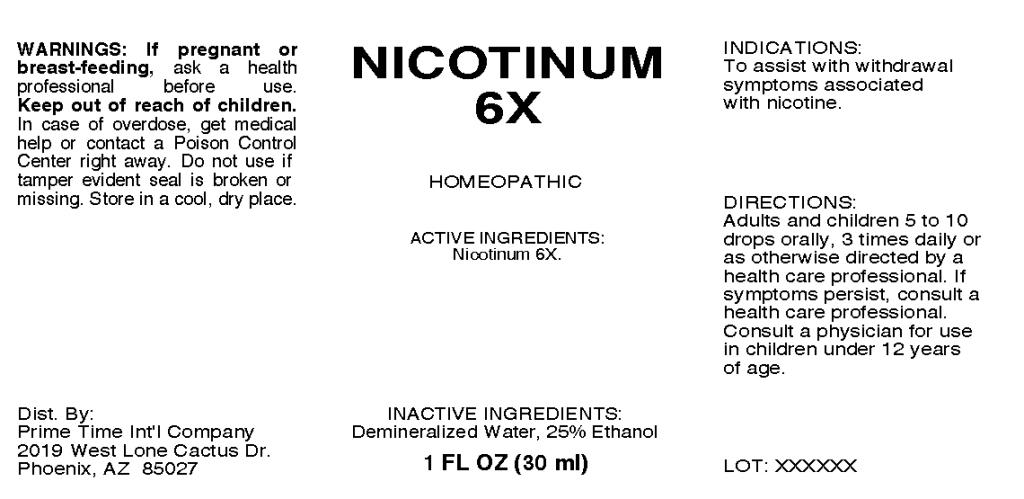 DRUG LABEL: Nicotinum
NDC: 57520-0615 | Form: LIQUID
Manufacturer: Apotheca Company
Category: homeopathic | Type: HUMAN OTC DRUG LABEL
Date: 20110317

ACTIVE INGREDIENTS: NICOTINE 6 [hp_X]/1 mL
INACTIVE INGREDIENTS: WATER; ALCOHOL

Nicotinum 6X

ACTIVE INGREDIENT: Nicotinum 6X.

PURPOSE

INDICATIONS: To assist with withdrawal symptoms associated with nicotine.

WARNINGS

WARNINGS: If pregnant or breast-feeding, ask a health professional before use.

Keep out of reach of children. In case of overdose, get medical help or contact a Poison Control Center right away.

Do not use if tamper evident seal is broken or missing. Store in a cool, dry place.

DOSAGE AND ADMINISTRATION

DIRECTIONS: Adults and children 5 to 10 drops orally, 3 times daily or as otherwise directed by a health care professional. If symptoms persist, consult a health care professional. Consult a physician for use in children under 12 years of age.

INACTIVE INGREDIENTS: Demineralized water, 25% Ethanol.

KEEP OUT OF REACH OF CHILDREN. In case of overdose, get medical help or contact a Poison Control Center right away.

INDICATIONS AND USAGE

INDICATIONS: To assist with withdrawal symptoms associated with nicotine.

QUESTIONS

Dist. By:

Prime Time Int'l Company

2019 West Lone Cactus Dr.

Phoenix, AZ 85027

PACKAGE LABEL

NICOTINUM 6X

HOMEOPATHIC

2 FL OZ (30 ml)